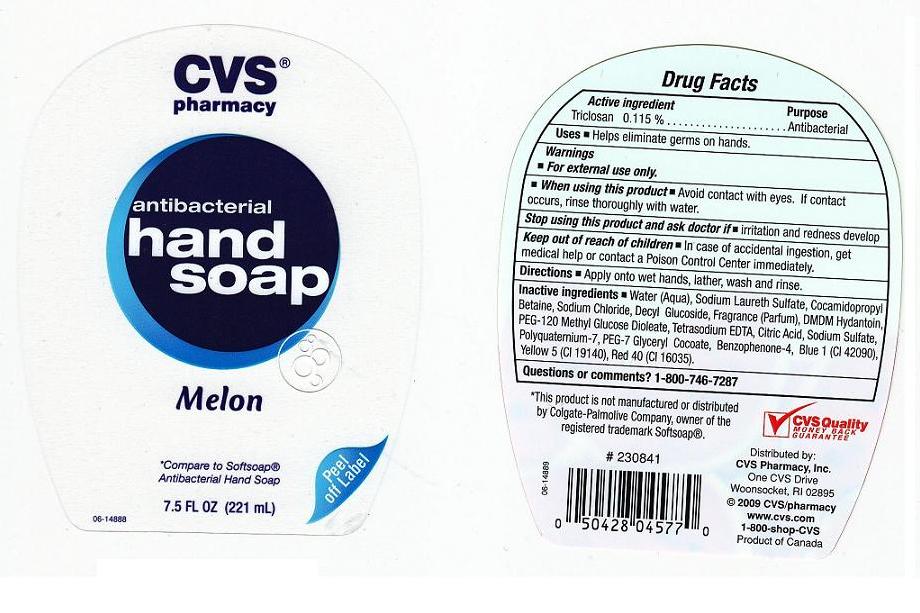 DRUG LABEL: CVS Phramacy Antibacterial
NDC: 59779-232 | Form: SOAP
Manufacturer: CVS Pharmacy 
Category: otc | Type: HUMAN OTC DRUG LABEL
Date: 20101001

ACTIVE INGREDIENTS: TRICLOSAN 0.115 mL/100 mL
INACTIVE INGREDIENTS: WATER; SODIUM LAURETH SULFATE; COCAMIDOPROPYL BETAINE; LAURYL GLUCOSIDE; SODIUM CHLORIDE; DMDM HYDANTOIN; PEG-120 METHYL GLUCOSE DIOLEATE; CITRIC ACID MONOHYDRATE; EDETATE SODIUM; SULISOBENZONE; SODIUM SULFATE; FD&C YELLOW NO. 5; FD&C BLUE NO. 1; FD&C RED NO. 40

Active Ingredient

Triclosan 0.115%

Purpose

Antibacterial

Uses

Helps eliminate germs on hands

Warning

For external use only.

When using this product

Avoid contact with eyes. If contact occurs, rinse thoroughly with water.

Stop using this product and ask doctor if

irritation and redness develop

Keep out of reach of children

In case of accidental ingestion, get medical help or contact a Poison Control Center immediately.

Directions

Apply onto wet hands, lather, wash and rinse.

Questions / Comments ?

1-800-746-7287

Inactive Ingredients

Water (Aqua), Sodium Laureth Sulfate, Cocamidopropyl Betaine, Decyl Glucoside, Sodium Chloride, Fragrance (Parfum), DMDM Hydantoin, PEG-120 Methyl Glucose Dioleate, Citric Acid, Tetrasodium EDTA, Benzophenone-4, Polyquaternium-7, PEG-7 Glyceryl Cocoate, Sodium Sulfate, Yellow 5 (CI 19140), Blue 1 (CI 42090), Red 40 (CI 16035)